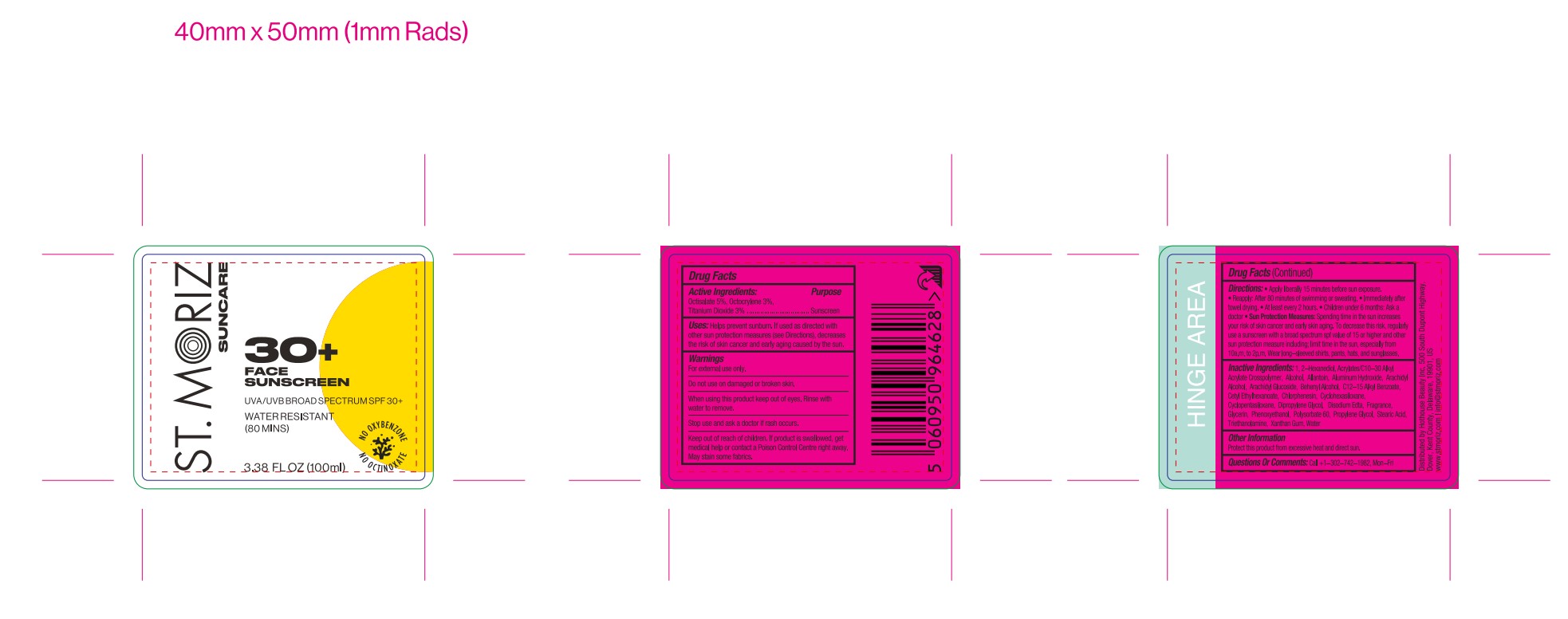 DRUG LABEL: St Moriz suncare face sunscreen spf30
NDC: 82723-015 | Form: LOTION
Manufacturer: Aopline Health Industry Technology (Guangzhou) Co., Ltd.
Category: otc | Type: HUMAN OTC DRUG LABEL
Date: 20250127

ACTIVE INGREDIENTS: OCTOCRYLENE 5.4 mg/180 mL; OCTISALATE 9 mg/180 mL; TITANIUM DIOXIDE 5.4 mg/180 mL
INACTIVE INGREDIENTS: CYCLOHEXASILOXANE; WATER; GLYCERIN; ALUMINUM HYDROXIDE; BEHENYL ALCOHOL; ARACHIDYL GLUCOSIDE; PHENOXYETHANOL; POLYSORBATE 60; CYCLOPENTASILOXANE; EDETATE DISODIUM; PROPYLENE GLYCOL; XANTHAN GUM; DIPROPYLENE GLYCOL; C12-15 ALKYL BENZOATE; ARACHIDYL ALCOHOL; ALLANTOIN; 1,2-HEXANEDIOL; ALCOHOL; STEARIC ACID; CHLORPHENESIN; TRIETHANOLAMINE; CETYL ETHYLHEXANOATE; ACRYLATES/C10-30 ALKYL ACRYLATE CROSSPOLYMER (60000 MPA.S)

Active Ingredients

OCTISALATE
TITANIUM DIOXIDE
OCTOCRYLENE

Purpose

Sunscreen

Uses

Uses: Helps prevent sunburn.

Warnings

For external use only .
Do not use on broken or damaged skin .
Stop use and ask a doctor if rash occurs
When using this product keep out of eyes . Rinse with water to remove .
Keep out of reach of children . If product is swallowed , get medical help or contact a
Poison Control Center right away .

Directions

Directions : Apply liberally 15 minutes before sun or water exposure. Works best on
moisturized skin.
Reapply:
After 80 minutes of swimming or sweating.
Immediately after towel drying.
At least every 2 hours.
Children under 6 months: Ask a doctor.

Inactive Ingredients

CYCLOHEXASILOXANE
WATER
CYCLOPENTASILOXANE
GLYCERIN
PROPYLENE GLYCOL
ALCOHOL
CETYL ETHYLHEXANOATE
ALUMINUM HYDROXIDE
STEARIC ACID
DIPROPYLENE GLYCOL
C12-15 ALKYL BENZOATE
ARACHIDYL ALCOHOL
BEHENYL ALCOHOL
ARACHIDYL GLUCOSIDE
PHENOXYETHANOL
1,2-HEXANEDIOL
CHLORPHENESIN
POLYSORBATE 60
ALLANTOIN
ACRYLATES/C10-30 ALKYL ACRYLATE CROSSPOLYMER
TRIETHANOLAMINE
XANTHAN GUM
DISODIUM EDTA

Keep out of reach of children . If product is swallowed , get medical help or contact a
Poison Control Center right away

Stop use

Stop use and ask a doctor if rash occurs
When using this product keep out of eyes . Rinse with water to remove .
When using this product keep out of eyes . Rinse with water to remove .
Keep out of reach of children . If product is swallowed , get medical help or contact a
Poison Control Center right away

Do not use on broken or damaged skin .
Stop use and ask a doctor if rash occurs

INDICATIONS AND USAGE

Directions : Apply liberally 15 minutes before sun or water exposure. Works best on
moisturized skin.
Reapply:
After 80 minutes of swimming or sweating.
Immediately after towel drying.
At least every 2 hours.
Children under 6 months: Ask a doctor.